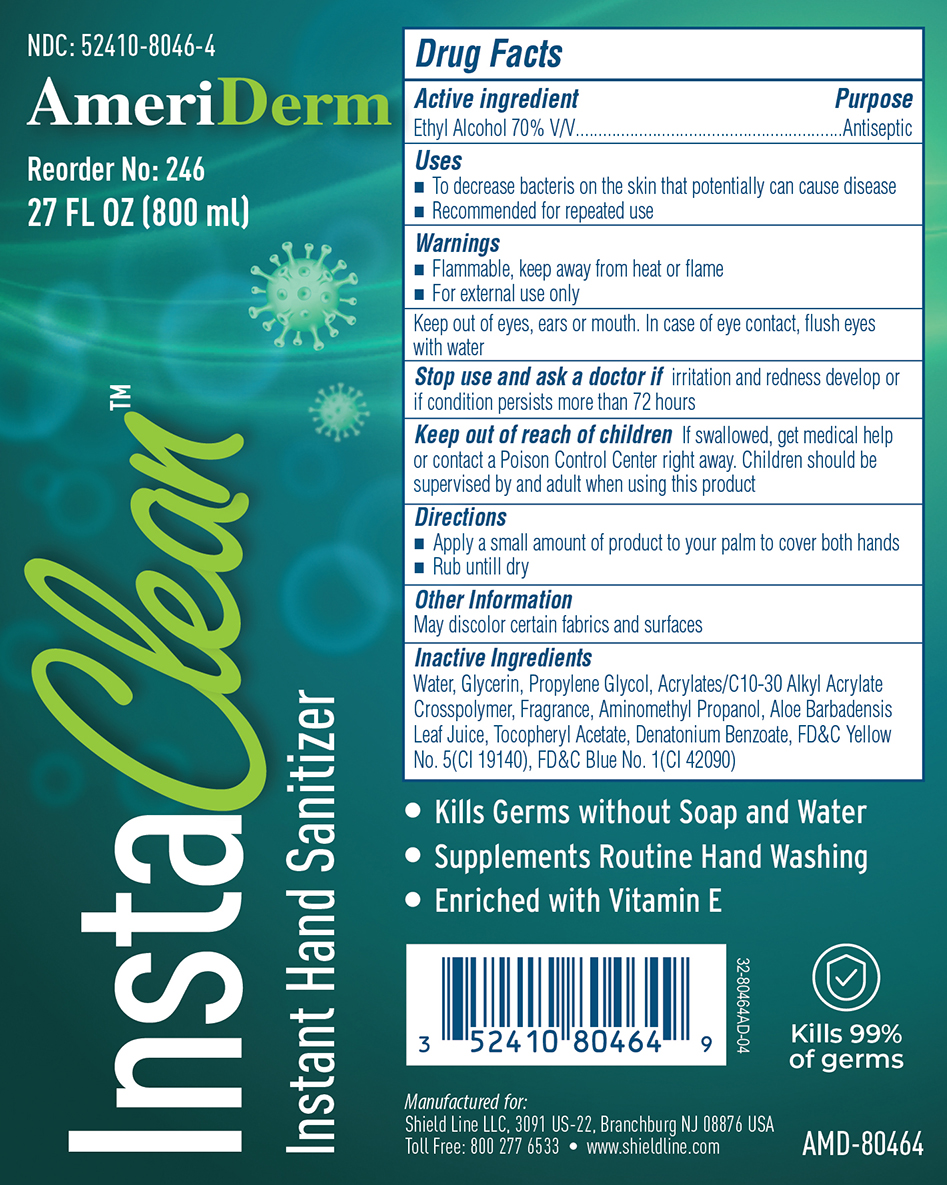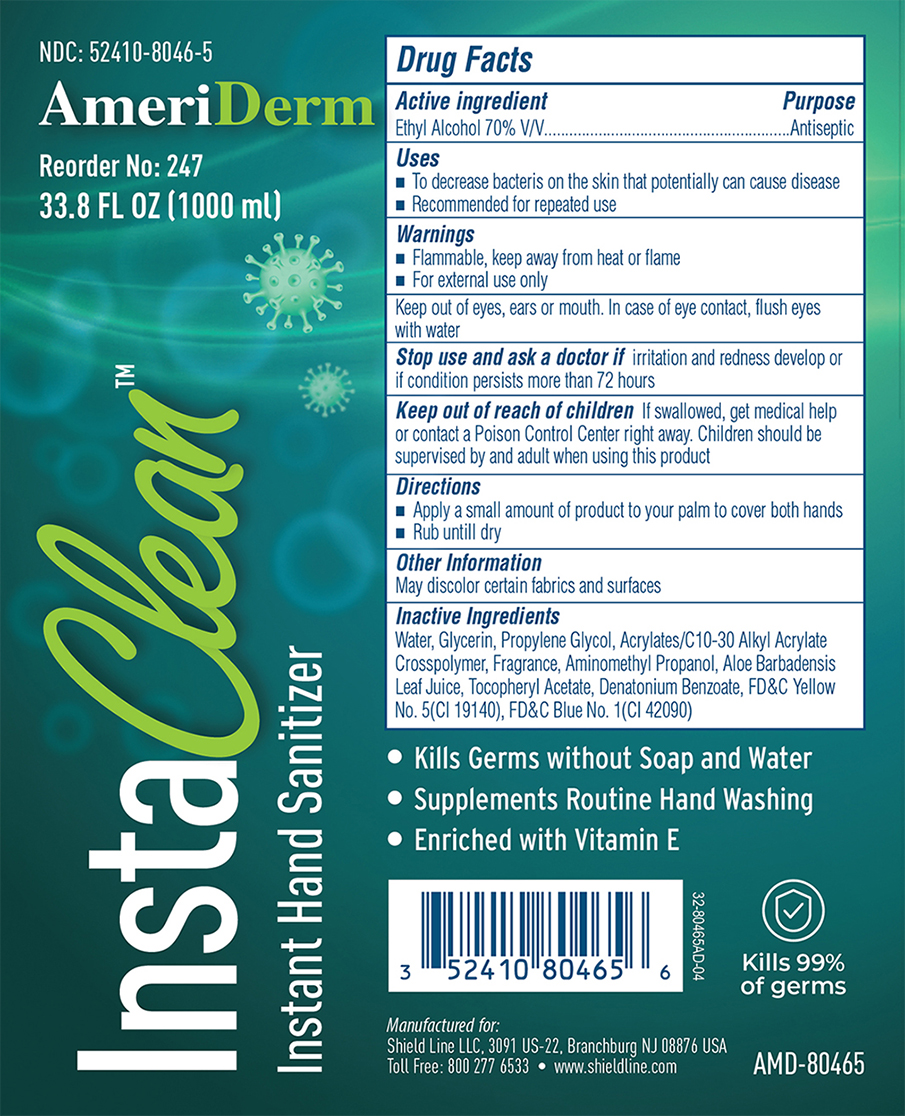 DRUG LABEL: INSTACLEAN
NDC: 52410-8046 | Form: GEL
Manufacturer: SHIELD LINE LLC
Category: otc | Type: HUMAN OTC DRUG LABEL
Date: 20260217

ACTIVE INGREDIENTS: ALCOHOL 70 mL/100 mL
INACTIVE INGREDIENTS: GLYCERIN; PROPYLENE GLYCOL; ALOE VERA LEAF; ACRYLATES/C10-30 ALKYL ACRYLATE CROSSPOLYMER (60000 MPA.S); AMINOMETHYL PROPANOL; FD&C BLUE NO. 1; .ALPHA.-TOCOPHEROL ACETATE; DENATONIUM BENZOATE; FD&C YELLOW NO. 5; WATER

INSTACLEAN

Active Ingredient

Ethyl Alcohol 70% v/v

Purpose

Antiseptic

Uses

- To decrease bacteria on the skin that potentially can cause disease.
- Recommended for repeated use.

Warnings

- Flammable, keep away from heat or flame
- For external use only

Keep out of eyes, ears or mouth. In case of eye contact, flush eyes with water

Stop use and ask a doctor

if irritation and redness develop or if condition persists more than 72 hours.

Keep out of reach of children.

If swallowed, get medical help or contact a Poison Control Center right away. Children should be supervised by an adult when using this product.

Directions

- Apply a small amount of product to your palm to cover both hands.
- Rub until dry.

Other Information

May discolor certain fabrics and surfaces.

Inactive Ingredients

Water, Glycerin, Propylene Glycol, Acrylates/c10-30 Alkyl Acrylate crosspolymer, Fragrance, Aminomethyl Propanol, Aloe Barbadensis Leaf Juice, Tocopherol Acetate, Denatonium Benzoate, FD&C Yellow No. 5, FD&C Blue No.1